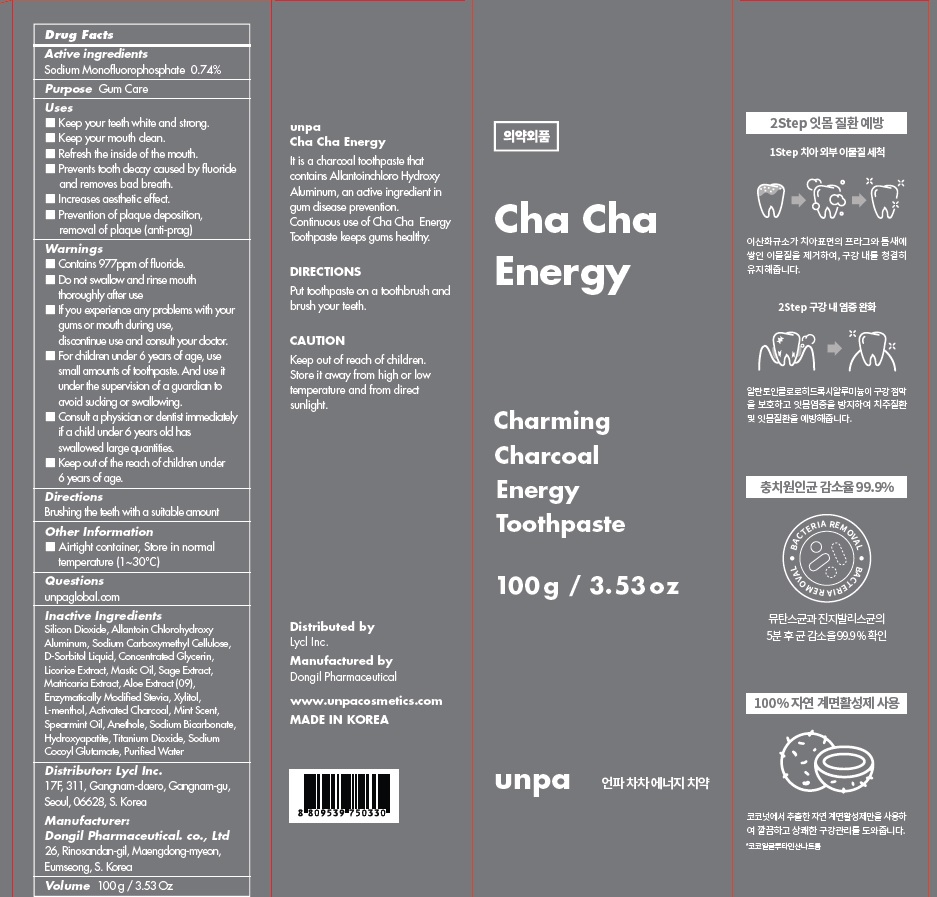 DRUG LABEL: unpa Cha Cha Energy Toothpaste
NDC: 73134-070 | Form: PASTE, DENTIFRICE
Manufacturer: Lycl Inc.
Category: otc | Type: HUMAN OTC DRUG LABEL
Date: 20210518

ACTIVE INGREDIENTS: Sodium Monofluorophosphate 0.74 g/100 g
INACTIVE INGREDIENTS: WATER; Sorbitol; Silicon Dioxide

ACTIVE INGREDIENT

Sodium Monofluorophosphate 0.74%

INACTIVE INGREDIENTS

Silicon Dioxide, Allantoin Chlorohydroxy Aluminum, Sodium Carboxymethyl Cellulose, D-Sorbitol Liquid, Concentrated Glycerin, Licorice Extract, Mastic Oil, Sage Extract, Matricaria Extract, Aloe Extract (09), Enzymatically Modified Stevia, Xylitol, L-menthol, Activated Charcoal, Mint Scent, Spearmint Oil, Anethole, Sodium Bicarbonate, Hydroxyapatite, Titanium Dioxide, Sodium Cocoyl Glutamate, Purified Water

PURPOSE

Gum Care

WARNINGS

■ Contains 977ppm of fluoride.
■ Do not swallow and rinse mouth thoroughly after use
■ If you experience any problems with your gums or mouth during use, discontinue use and consult your doctor.
■ For children under 6 years of age, use small amounts of toothpaste. And use it under the supervision of a guardian to avoid sucking or swallowing.
■ Consult a physician or dentist immediately if a child under 6 years old has swallowed large quantities.
■ Keep out of the reach of children under 6 years of age.

KEEP OUT OF REACH OF CHILDREN

■ Keep out of the reach of children under 6 years of age.

Uses

■ Keep your teeth white and strong.
■ Keep your mouth clean.
■ Refresh the inside of the mouth.
■ Prevents tooth decay caused by fluoride and removes bad breath.
■ Increases aesthetic effect.
■ Prevention of plaque deposition, removal of plaque (anti-prag)

Directions

Brushing the teeth with a suitable amount

Other Information

■ Airtight container, Store in normal temperature (1~30℃)

QUESTIONS

■ unpaglobal.com